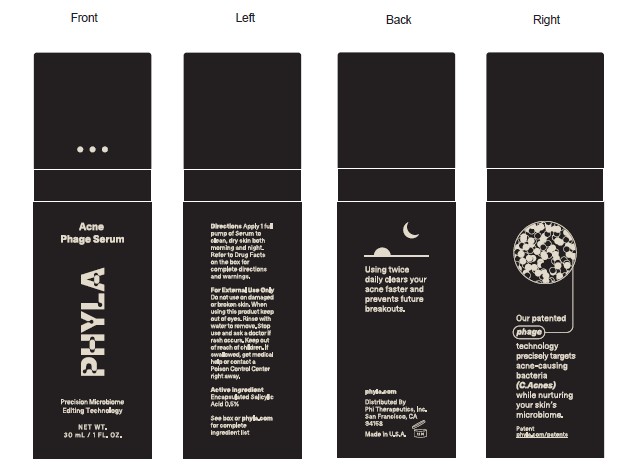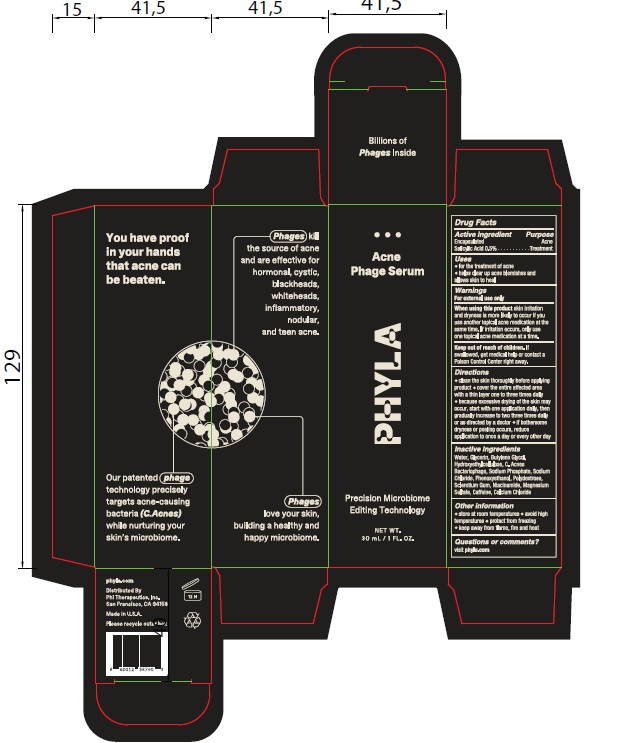 DRUG LABEL: PHYLA ACNE PHAGE SERUM
NDC: 68577-230 | Form: LOTION
Manufacturer: COSMAX USA, CORP
Category: otc | Type: HUMAN OTC DRUG LABEL
Date: 20251231

ACTIVE INGREDIENTS: SALICYLIC ACID 5 mg/100 mL
INACTIVE INGREDIENTS: CAFFEINE; CALCIUM CHLORIDE; POLYDEXTROSE; GLYCERIN; SCLEROTIUM GUM; NIACINAMIDE; MAGNESIUM SULFATE; BUTYLENE GLYCOL; WATER; HYDROXYETHYLCELLULOSE; LISTERIA VIRUS P100; SODIUM PHOSPHATE; SODIUM CHLORIDE; PHENOXYETHANOL

PHYLA ACNE PHAGE SERUM

Active ingredient

Salicilic Acid 0.5%

Purpose

Acne Treatment

USES

- for the treatment of acne
- helps clear up acne blemishes and allows skin to heal

WARNINGS

For external use only

When using this product skin irritation and dryness is more likely to occur if you use another topical acne medication at the same time. If irritation occurs, only use one topical acne medication at a time.

Keep out of reach of children. If swallowed get medical help or contact a Poison Control Center right away.

DIRECTIONS

- clean the skin thoroughly before applying product
- cover the entire affected area with a thin layer one to three times daily
- because excessive drying of the skin may occur, start with one application daily, then gradually increase to two three times daily or as directed by a doctor
- if bothersome dryness or peeling occurs, reduce application to once a day or every other day

Inactive ingredients

Water, Glycerin, Butylene Glycol, Hydroxyethylcellulose, C. Acnes Bacteriophage, Sodium Phosphate, Sodium Chloride, Phenoxyethanol, Polydextrose, Sclerotium Gum, Niacinamide, Magnesium Sulfate, Caffeine, Calcium Chloride.

OTHER INFORMATION

- store at room temperature
- avoid high temperatures
- protect from freezing
- keep away from flame, fire and heat

Questions or comments?

visit phyla.com